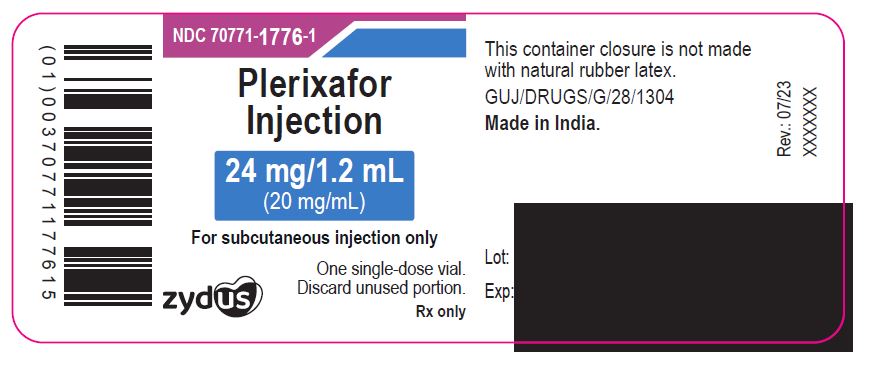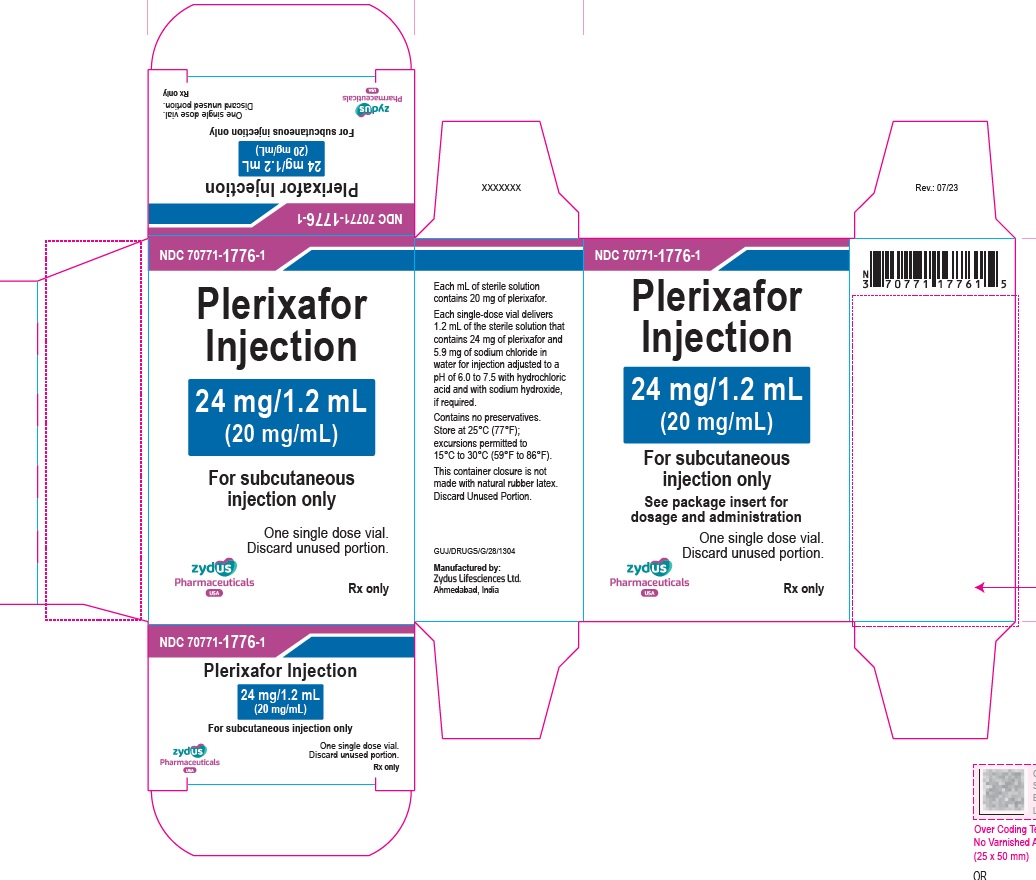 DRUG LABEL: PLERIXAFOR
NDC: 70771-1776 | Form: INJECTION
Manufacturer: Zydus Lifesciences Limited
Category: prescription | Type: HUMAN PRESCRIPTION DRUG LABEL
Date: 20230728

ACTIVE INGREDIENTS: PLERIXAFOR 24 mg/1.2 mL
INACTIVE INGREDIENTS: HYDROCHLORIC ACID; SODIUM CHLORIDE 5.9 mg/1.2 mL; SODIUM HYDROXIDE; WATER

PLERIXAFOR injection, for subcutaneous use

PACKAGE LABEL.PRINCIPAL DISPLAY PANEL

NDC 70771-1776-1

Plerixafor Injection – 1.2 mL vial label

24 mg/1.2 mL

(20 mg/mL)

For subcutaneous injection only

For single-dose only

Rx only

NDC 70771-1776-1

Carton contains one vial of

Plerixafor Injection

24 mg/1.2 mL

(20 mg/mL)

For subcutaneous injection only

See package insert for dosage and administration

For single-dose only

Rx only